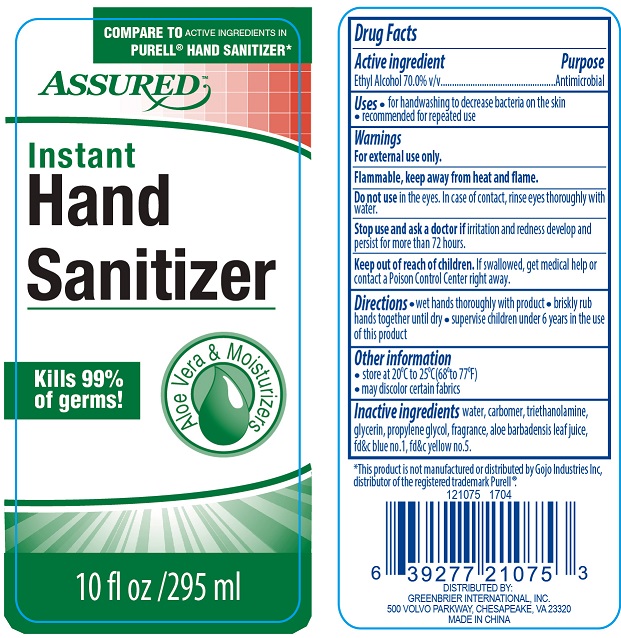 DRUG LABEL: Assured Aloe
NDC: 58503-095 | Form: GEL
Manufacturer: China Ningbo Shangge Cosmetic Technology Corp.
Category: otc | Type: HUMAN OTC DRUG LABEL
Date: 20190918

ACTIVE INGREDIENTS: ALCOHOL 70 mL/100 mL
INACTIVE INGREDIENTS: WATER; CARBOMER COPOLYMER TYPE A; TROLAMINE; GLYCERIN; PROPYLENE GLYCOL; ALOE VERA LEAF; FD&C BLUE NO. 1; FD&C YELLOW NO. 5

Assured Aloe

Active Ingredient Purpose

Ethyl Alcohol 70.0% v/v..................... Antimicrobial

Uses

- for handwashing to decrease bacteria on the skin
- recommended for repeated use

Keep out of reach of children. If swallowed, get medical help or contact a Poison Control Center right away.

INDICATIONS AND USAGE

Assured

Instant Hand Sanitizer

Kills 99% of germs!

Aloe Vera & Moisturizers

Compare to Active Ingredients in Purell® Hand Sanitizer*

Special Value 25% more free

10 fl oz / 295 ml

*This product is not manufactured or distributed by Gojo Industries Inc, distributor of the registered trademark Purell

Directions

- wet hands thoroughly with product
- briskly rub hands together until dry
- supervise children under 6 years in the use of this product

Warnings

For external use only.

Flammable, keep away from heat and flame.

Do not use in the eyes. In case of contact, rinse eyes thoroughly with water.

Stop use and ask a doctor if irritation and redness develop and persist for more than 72 hours.

Inactive Ingredients

water, carbomer, triethanolamine, glycerin, propylene glycol, fragrance, aloe barbadensis leaf juice, fd&c blue no. 1, fd&c yellow no. 5.